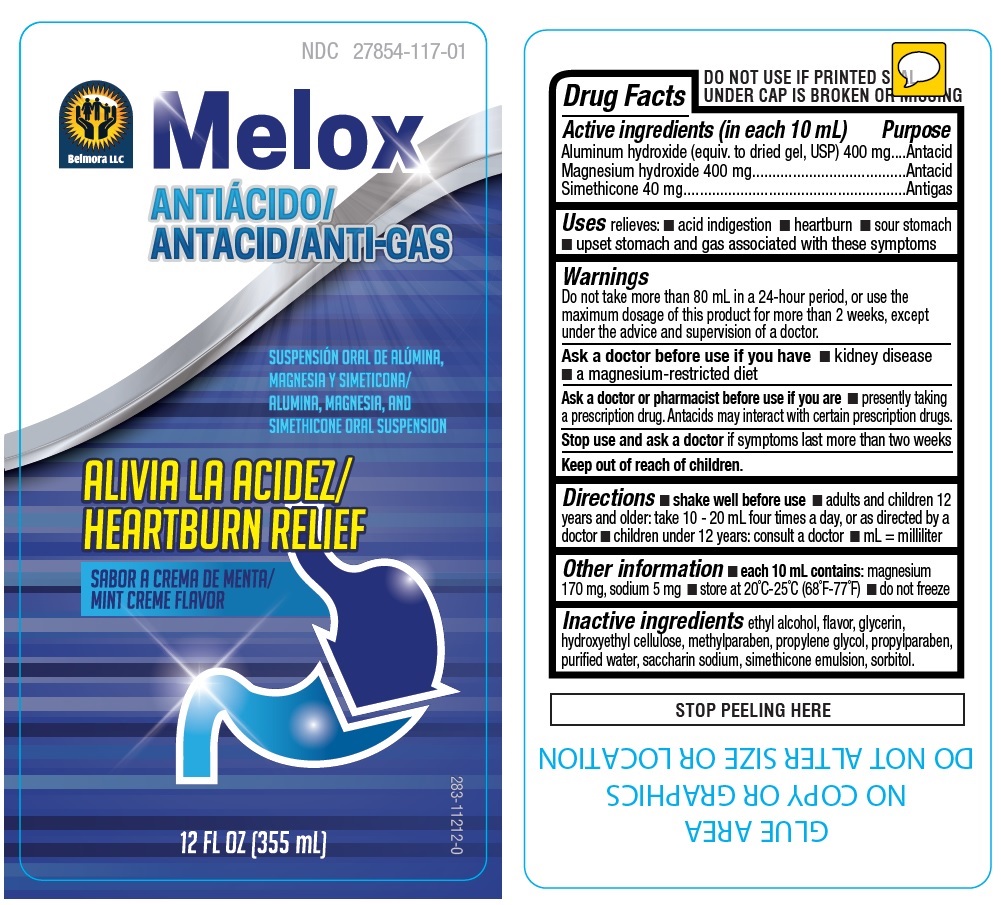 DRUG LABEL: Melox
NDC: 27854-117 | Form: LIQUID
Manufacturer: Belmora LLC
Category: otc | Type: HUMAN OTC DRUG LABEL
Date: 20241004

ACTIVE INGREDIENTS: ALUMINUM HYDROXIDE 400 mg/10 mL; MAGNESIUM HYDROXIDE 400 mg/10 mL; DIMETHICONE 40 mg/10 mL
INACTIVE INGREDIENTS: ALCOHOL; GLYCERIN; HYDROXYETHYL CELLULOSE, UNSPECIFIED; METHYLPARABEN; PROPYLENE GLYCOL; PROPYLPARABEN; WATER; SACCHARIN SODIUM; SORBITOL

Melox

Active ingredients (in each 10 mL)

Aluminum hydroxide (equiv. to dried gel, USP) 400 mg
Magnesium hydroxide 400 mg
Simethicone 40 mg

Purpose

Antacid
Antacid
Antigas

Uses

relieves: • acid indigestion • heartburn • sour stomach • upset stomach and gas associated with these symptoms

Warnings

Do not take more than 80 mL in a 24-hour period, or use the maximum dosage of this product for more than 2 weeks, except under the advice and supervision of a doctor.

Ask a doctor before use if you have • kidney disease • a magnesium-restricted diet

Ask a doctor or pharmacist before use if you are • presently taking a prescription drug. Antacids may interact with certain prescription drugs.

Stop use and ask a doctor if symptoms last more than two weeks

Keep out of reach of children.

Directions

• shake well before use • adults and children 12 years and older: take 10 - 20 mL four times a day, or as directed by a doctor • children under 12 years: consult a doctor • mL = milliliter

Other information

• each 10 mL contains: magnesium 170 mg, sodium 5 mg • store at 20°C-25°C (68°F-77°F) • do not freeze

Inactive ingredients

ethyl alcohol, flavor, glycerin, hydroxyethyl cellulose, methylparaben, propylene glycol, propylparaben, purified water, saccharin sodium, simethicone emulsion, sorbitol.

Belmora LLC

ALUMINA, MAGNESIA, AND SIMETHICONE ORAL SUSPENSION

HEARTBURN RELIEF

MINT CREME FLAVOR

DO NOT USE IF PRINTED SEAL UNDER CAP IS BROKEN OR MISSING